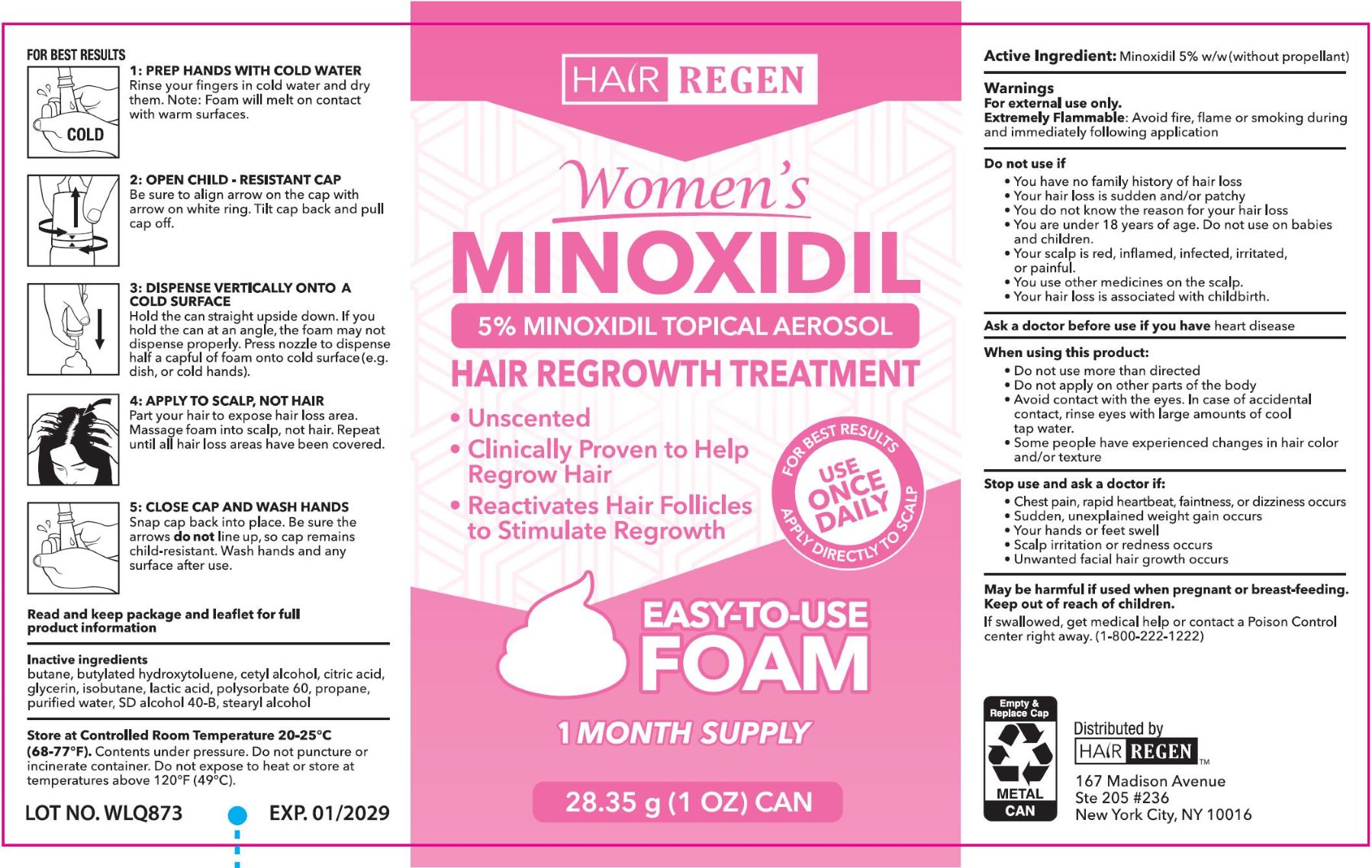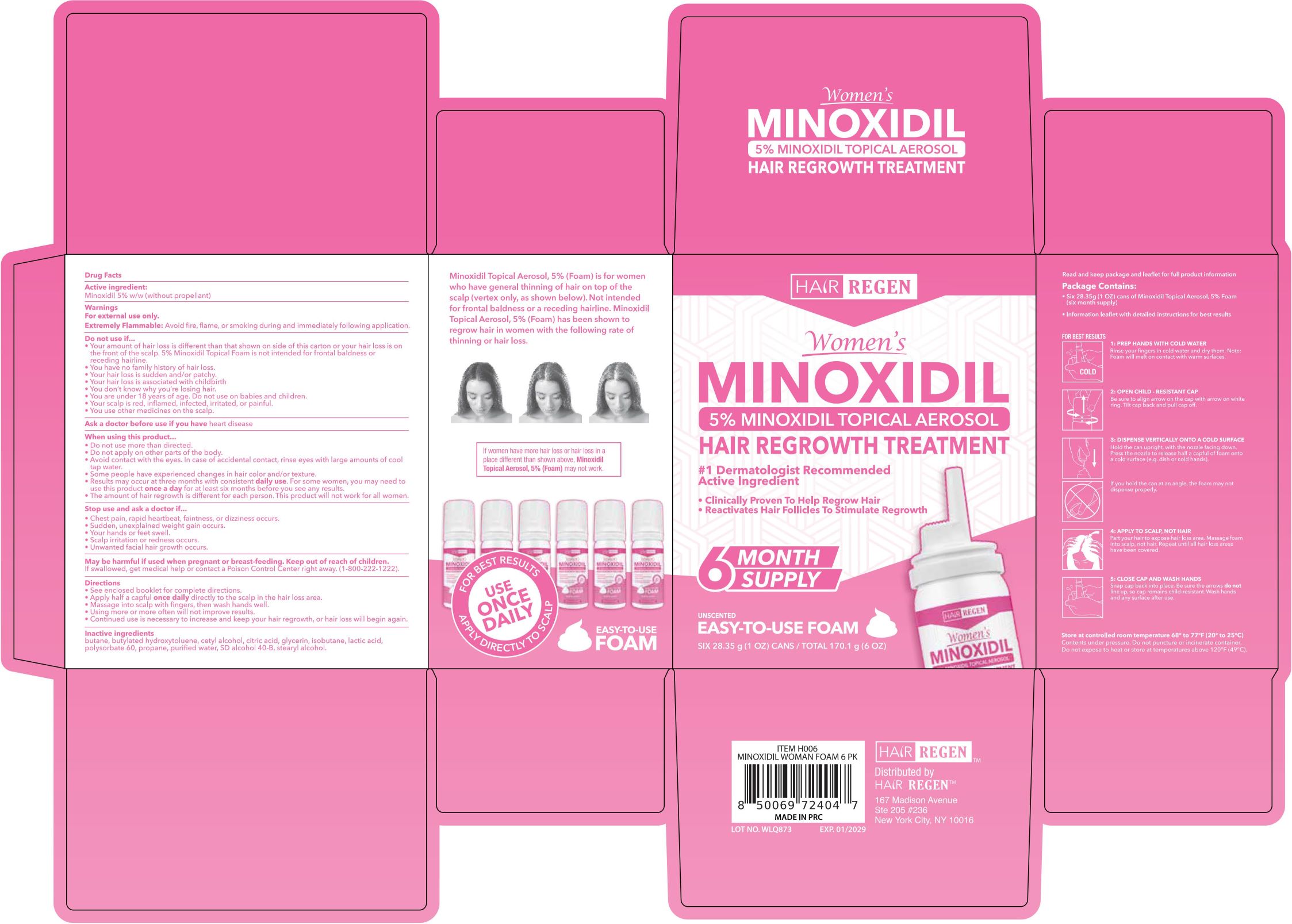 DRUG LABEL: Hair Regen - Hair Regrowth Treatment
NDC: 84232-018 | Form: AEROSOL, FOAM
Manufacturer: Yiwu Yizhou Trading Co., Ltd
Category: otc | Type: HUMAN OTC DRUG LABEL
Date: 20250415

ACTIVE INGREDIENTS: MINOXIDIL 5 g/100 g
INACTIVE INGREDIENTS: GLYCERIN; BUTANE; WATER; ALCOHOL; LACTIC ACID; POLYSORBATE 60; ISOBUTANE; STEARYL ALCOHOL; PROPANE; CETYL ALCOHOL; BUTYLATED HYDROXYTOLUENE; CITRIC ACID

Minoxidil 5% for Hair Regen Womens foam Minoxidil 6 pk

Active Ingredient

Minoxidil 5% w/w (without propellant)

Purpose

Hair regrowth treatment

Use

for women who have general thinning of hair on top of the scalp (vertex only, as shown below).

Warnings

For external use only. For use by men only.

Extremely Flammable: Avoid fire, flame, or smoking during and immediately following application.

Do not use if

- your amount of hair loss is different than that shown on the side of this carton or your hair loss is on the front of the scalp. 5% minoxidil topical foam is not intended for frontal baldness or receding hairline.
- you have no family history of hair loss.
- your hair loss is sudden and/or patchy.
- you do not know the reason for your hair loss.
- you are under 18 years of age. Do not use on babies and children.
- your scalp is red, inflamed, infected, irritated, or painful.
- you use other medicines on the scalp.

Ask a doctor before use

if you have heart disease

When using this product

- do not use more than directed.
- do not apply on other parts of the body.
- avoid contact with the eyes. In case of accidental contact, rinse eyes with large amounts of cool tap water.
- some people have experienced changes in hair color and/or texture.
- results may occur at three months with consistent daily use. For some women, you may need to use this product once a day for at least six months before you see results.
- the amount of hair regrowth is different for each person. This product will not work for all women.

Stop use and ask a doctor if ...

- chest pain, rapid heartbeat, faintness, or dizziness occurs.
- sudden, unexplained weight gain occurs.
- your hands or feet swell.
- scalp irritation or redness occurs.
- unwanted facial hair growth occurs.

Keep out of reach of children.

If swallowed, get medical helf or contact a Poison Control Center right away.

Directions

- see enclosed booklet for complete directions.
- apply half a capful once daily directly to the scalp in the hair loss area.
- massage into scalp with fingers, then wash hands well.
- using more or more often will not improve results.
- continued use is necessary to increase and keep your hair regrowth, or hair loss will begin again.

STORAGE AND HANDLING

Store at controlled room temperature 68-77℉ (20-25℃).

Contents under pressure. Do not puncture or incinerate container. Do not expose to heat or store at temperaures above 120℉ (49℃).

Inactive ingredients

butane, butylated hydroxytoluene, cetyl alcohol, citric acid, glycerin, isobutane, lactic acid, polysorbate 60, propane, purified water, SD alcohol 40-B, stearyl alcohol.

PACKAGE LABEL

W19:

W-01: